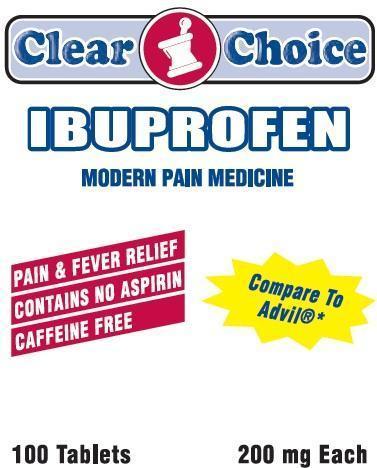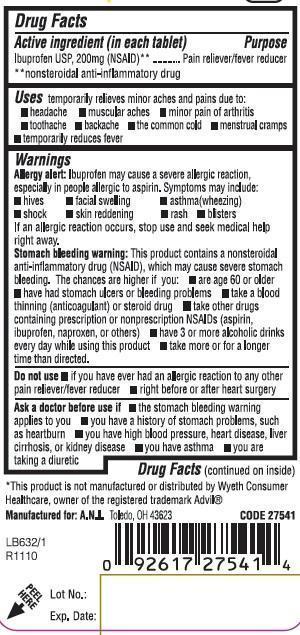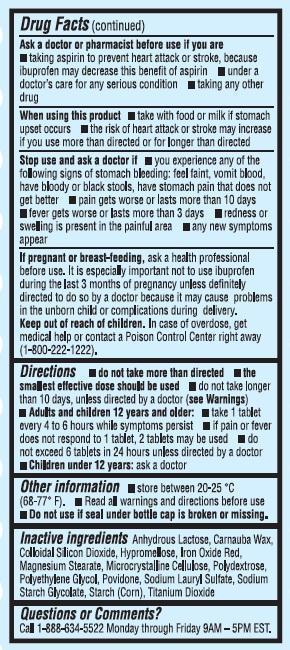 DRUG LABEL: Clear Choice Ibuprofen
NDC: 53185-003 | Form: TABLET
Manufacturer: Athlete's Needs Inc
Category: otc | Type: HUMAN OTC DRUG LABEL
Date: 20161107

ACTIVE INGREDIENTS: IBUPROFEN 200 mg/1 1
INACTIVE INGREDIENTS: ANHYDROUS LACTOSE; CARNAUBA WAX; SILICON DIOXIDE; HYPROMELLOSES; FERRIC OXIDE RED; MAGNESIUM STEARATE; CELLULOSE, MICROCRYSTALLINE; POLYDEXTROSE; POLYETHYLENE GLYCOLS; POVIDONES; SODIUM LAURYL SULFATE; STARCH, CORN; TITANIUM DIOXIDE

Clear Choice Ibuprofen

Active ingredient (in each tablet)

Ibuprofen USP, 200mg (NSAID)
nonsteroidal anti-inflammatory drug

Purpose

Pain reliever/fever reducer

Uses

temporarily relieves minor aches and pains due to

- headache
- muscular aches
- minor pain of arthritis
- toothache
- backache
- the common cold
- menstrual cramps
- temporarily reduces fever

Warnings

Allergy alert: Ibuprofen may cause a severe allergic reaction, especially in people allergic to aspirin. Symptoms may include:

- hives
- facial swelling
- asthma (wheezing)
- shock
- skin reddening
- rash
- blisters

If an allergic reaction occurs, stop use and seek medical help right away.

Stomach bleeding warning

: This product contains a nonsteroidal anti-inflammatory drug (NSAID), which may cause severe stomach bleeding. The chances are higher if you:

- are age 60 or older
- have had stomach ulcers or bleeding problems
- take a blood thinning (anticoagulant) or steroid drug
- take other drugs containing prescription or nonprescription NSAIDs (aspirin, ibuprofen, naproxen, or others)
- have 3 or more alcoholic drinks every day while using this product
- take more or for a longer time than directed

Do not use

if you have ever had an allergic reaction to other pain reliever/fever reduce

right before or after heart surgery

Ask a doctor before use if

- the stomach bleeding warning applies to you
- you have a history of stomach problems, such as heartburn
- you have high blood pressure, heart disease, liver cirrhosis, or kidney disease
- you have asthma
- you are taking a diuretic

Ask a doctor or pharmacist before use if you are

- taking aspirin to prevent heart attack or stroke, because ibuprofen may decrease this benefit of aspirin
- under a doctor's care for any serious condition
- taking any other drug

When using this product

- take with food or milk if stomach upset occurs
- the risk of heart attack or stroke may increase if you use more than directed or for longer than directed

Stop use and ask a doctor if

- you experience any of the following signs of stomach bleeding: feel faint, vomit blood, have bloody or black stools, have stomach pain that does not get better
- pain gets worse or lasts more than 10 days
- fever gets worse or lasts more than 3 days
- redness or swelling is present in the painful area
- any new symptoms appear

If pregnant or breast-feeding

ask a health professional before use. It is especially important not to use ibuprofen during the last 3 months of pregnancy unless definitely directed to do so by a doctor because it may cause problems in the unborn child or complications during delivery.

Keep out of reach of children.

In case of overdose, get medical help or contact a Poison Control center right away (1-800-222-1222).

Directions

- do not take more than directed
- the smallest effective dose should be used
- do not take longer than 10 days, unless directed by a doctor (see Warnings)
- Adults and children 12 years and older:
- take 1 tablet every 4 to 6 hours while symptoms persist
- if pain or fever does not respond to 1 tablet, 2 tablets may be used
- do not exceed 6 tablets in 24 hours unless directed by a doctor
- Children under 12 years: ask a doctor

Other information

- store between 20-25 degrees Celsius (68-77 degrees Fahrenheit).
- Read all warnings and directions before use
- Do not use if seal under bottle cap is broken or missing.

Inactive ingredients

Anhydrous Lactose, Carnauba Wax, Colloidal Silicon Dioxide, Hypromellose, Iron Oxide Red, Magnesium Stearate, Microcrystalline Cellulose, Polydextrose, Polyethylene Glycol, Povidone, Sodium Lauryl Sulfate, Sodium Starch Glycolate, Starch (Corn), Titanium Dioxide

Questions or Comments

Call 1-888-634-5522 Monday through Friday 9AM - 5PM EST.

Package Label

Clear Choice

IBUPROFEN

MODERN PAIN MEDICINE

PAIN AND FEVER RELIEF
CONTAINS NO ASPIRIN
CAFFEINE FREE

Compare to Advil (R)

100 Tablets
200 mg each

This product is not manufactured or distributed by Wyeth Consumer Healthcare, owner of the registered trademark Advil (R)

Manufactured for: A.N.I. Toledo, OH 43623 CODE 27541

Lot No.:

Exp. Date: